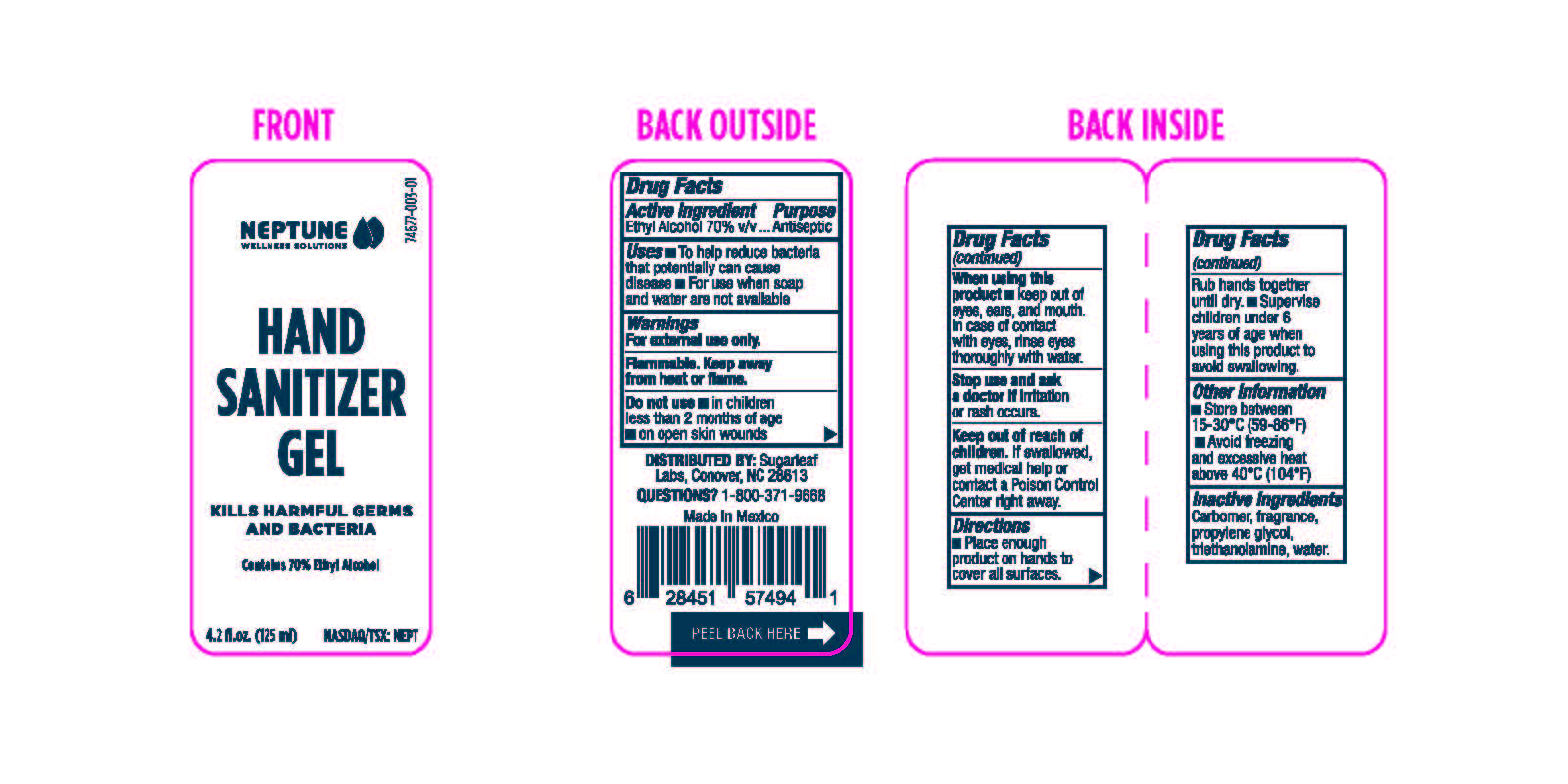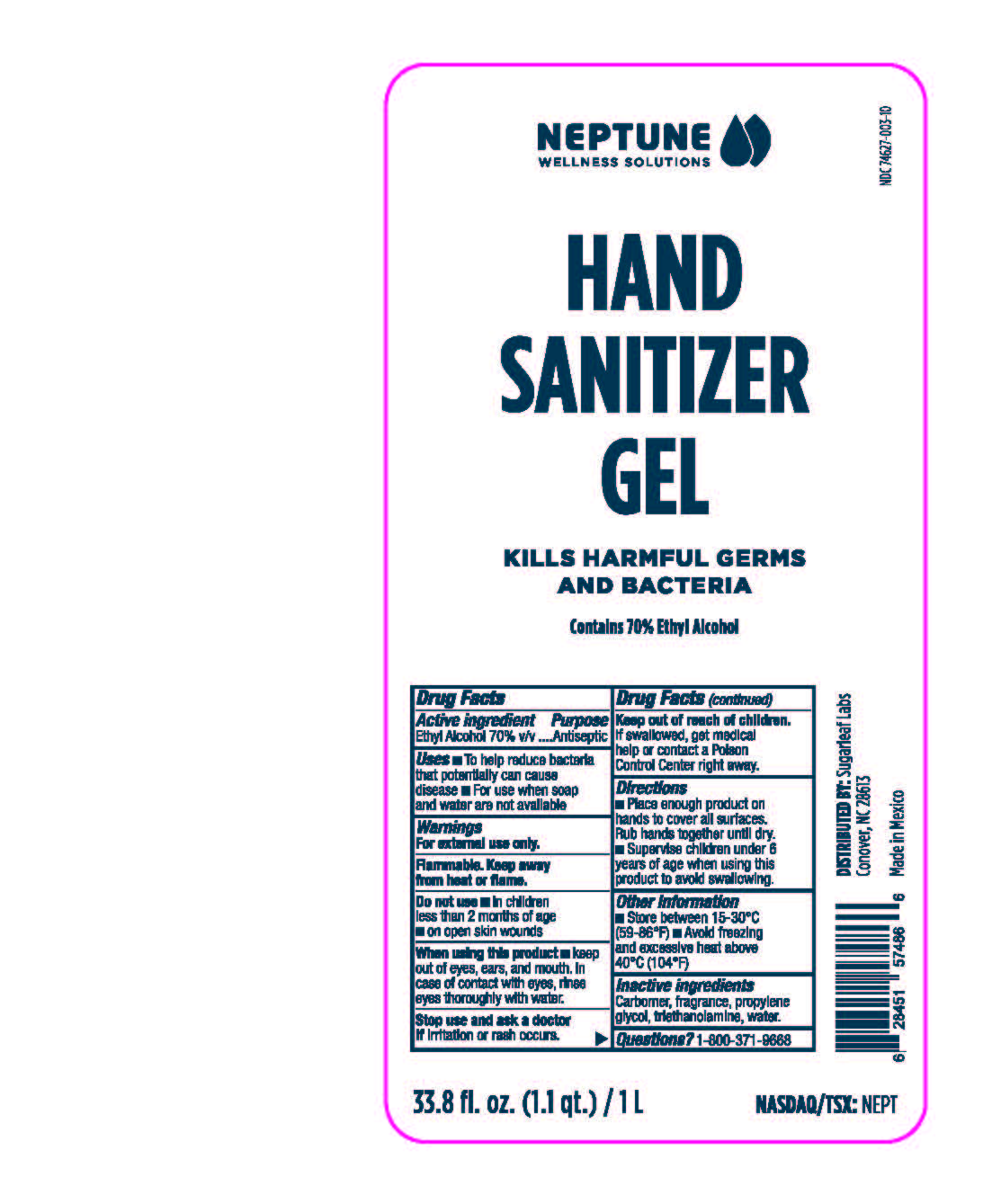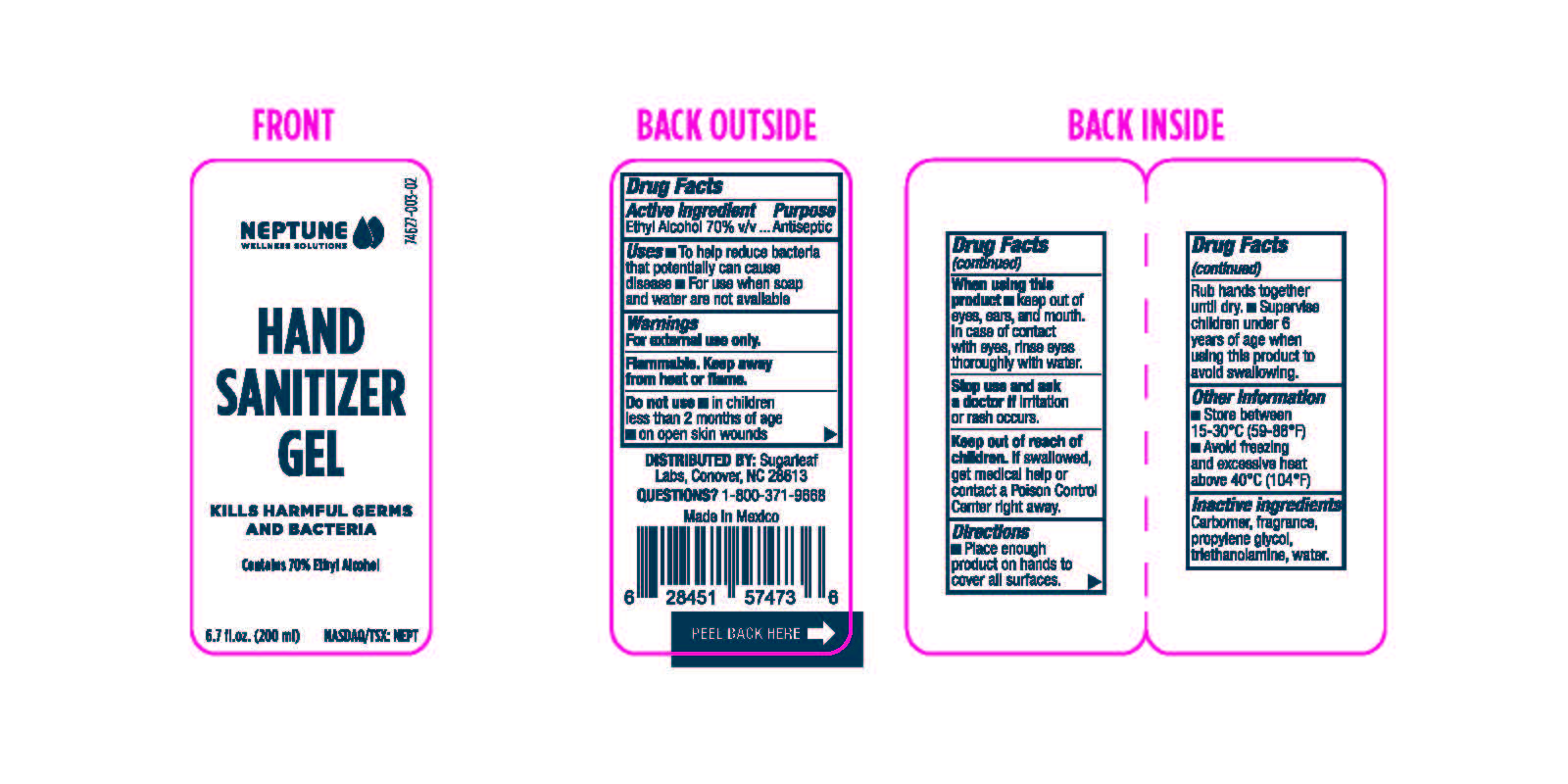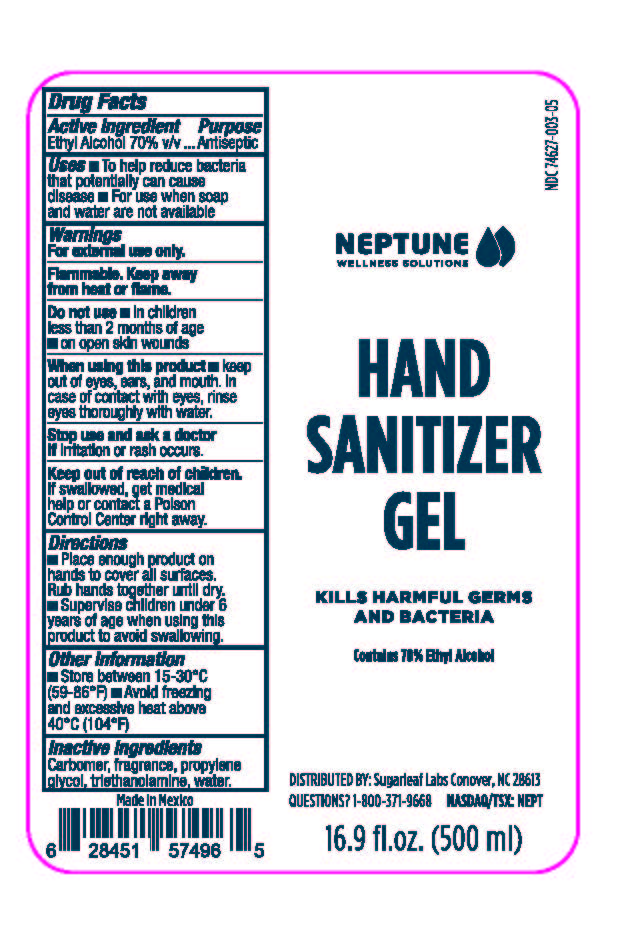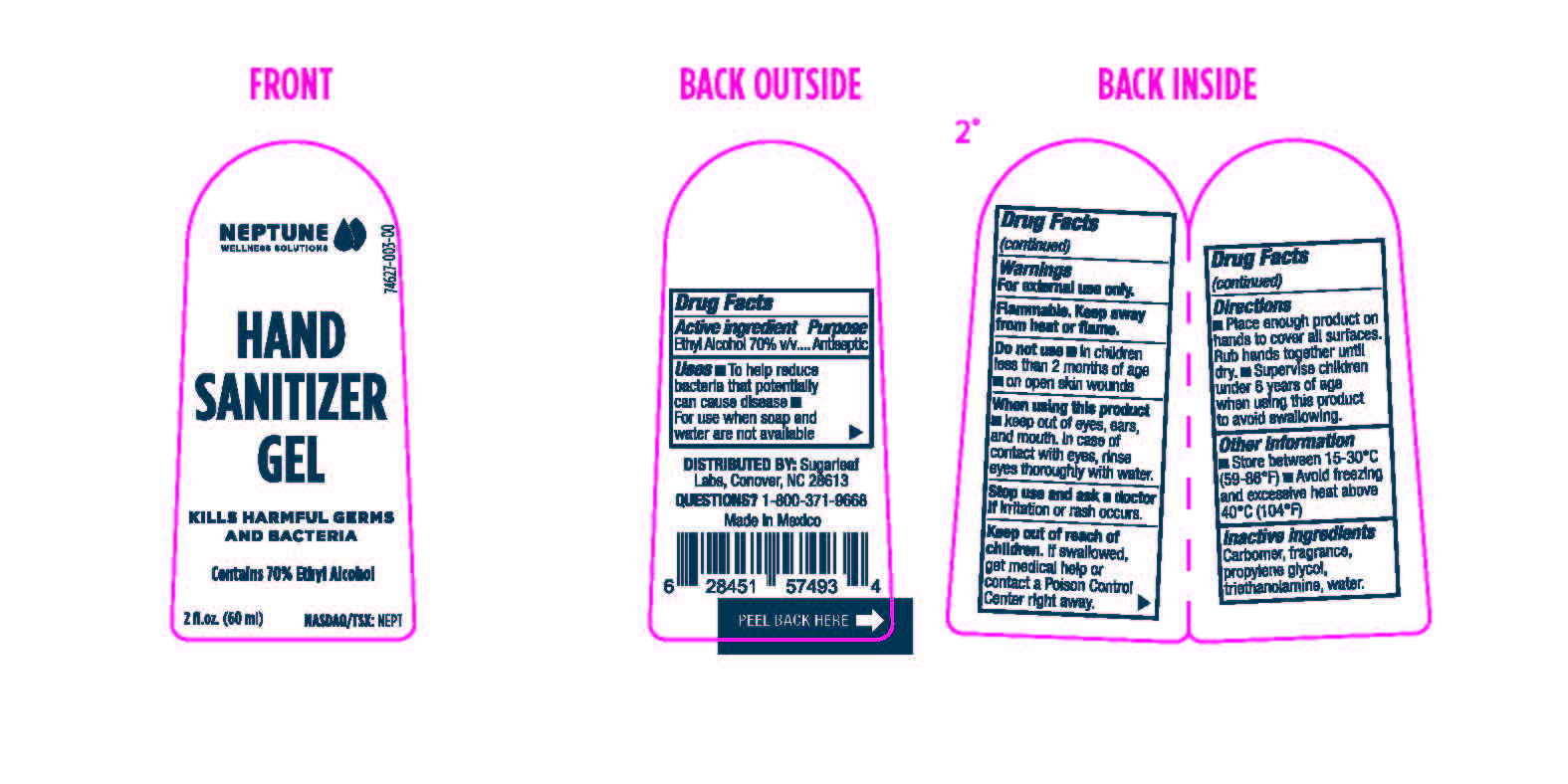 DRUG LABEL: Hand Sanitizer
NDC: 74627-003 | Form: GEL
Manufacturer: Sugarleaf Labs Inc.
Category: otc | Type: HUMAN OTC DRUG LABEL
Date: 20200707

ACTIVE INGREDIENTS: ALCOHOL 70 mL/100 mL
INACTIVE INGREDIENTS: CARBOMER HOMOPOLYMER, UNSPECIFIED TYPE 1 mL/100 mL; PROPYLENE GLYCOL 8 mL/100 mL; TROLAMINE 1 mL/100 mL; WATER 20 mL/100 mL

Hand sanitizer

Active Ingredient(s)

Alcohol 70% v/v. Purpose: Antiseptic

Purpose

Antiseptic, Hand Sanitizer

Use

Hand Sanitizer to help reduce bacteria that potentially can cause disease. For use when soap and water are not available.

Warnings

For external use only. Flammable. Keep away from heat or flame

Do not use

- in children less than 2 months of age
- on open skin wounds

When using this product keep out of eyes, ears, and mouth. In case of contact with eyes, rinse eyes thoroughly with water.
Stop use and ask a doctor if irritation or rash occurs. These may be signs of a serious condition.
Keep out of reach of children. If swallowed, get medical help or contact a Poison Control Center right away.

Stop use and ask a doctor if irritation or rash occurs. These may be signs of a serious condition.

Keep out of reach of children. If swallowed, get medical help or contact a Poison Control Center right away.

Directions

- Place enough product on hands to cover all surfaces. Rub hands together until dry.
- Supervise children under 6 years of age when using this product to avoid swallowing.

Other information

- Store between 15-30C (59-86F)
- Avoid freezing and excessive heat above 40C (104F)

Inactive ingredients

carbomer, fragrance, propylene glycol, triethanolamine, water.

RECENT MAJOR CHANGES

Effective date was changed from March 28, 2020 (draft listing) to May 13, 2020. This is the first listing of this product so this change is irrelevant.

Package Label - Principal Display Panel

33.8 fl. oz. (1.1 qt.) / 1 L NDC: 74627-003-10

16.9 fl. oz. (500 mL) NDC: 74627-003-05

6.7 fl. oz. (200 mL) NDC: 74627-003-02

4.2 fl. oz. (125 mL) NDC: 74627-003-01

2 fl. oz. (60 mL) NDC: 74627-003-00